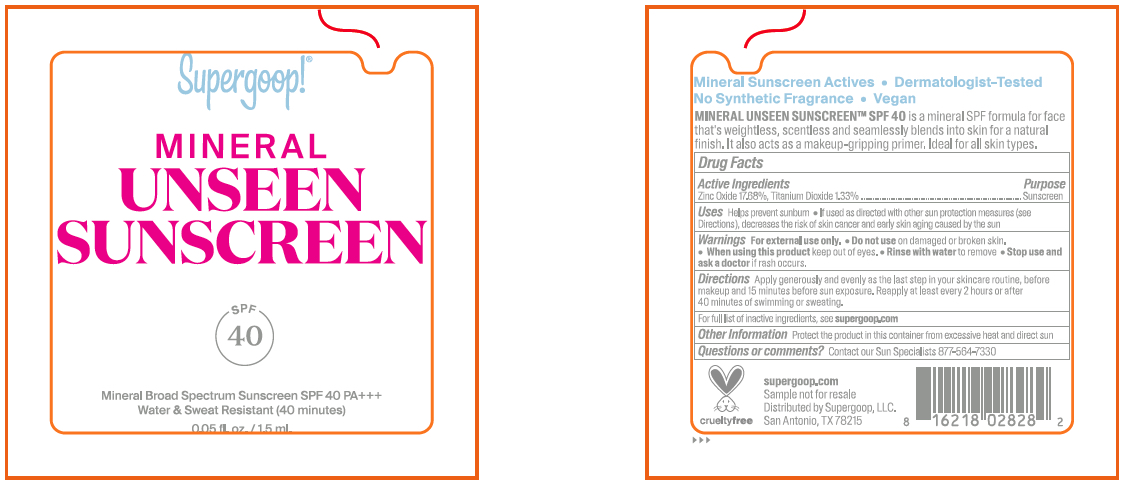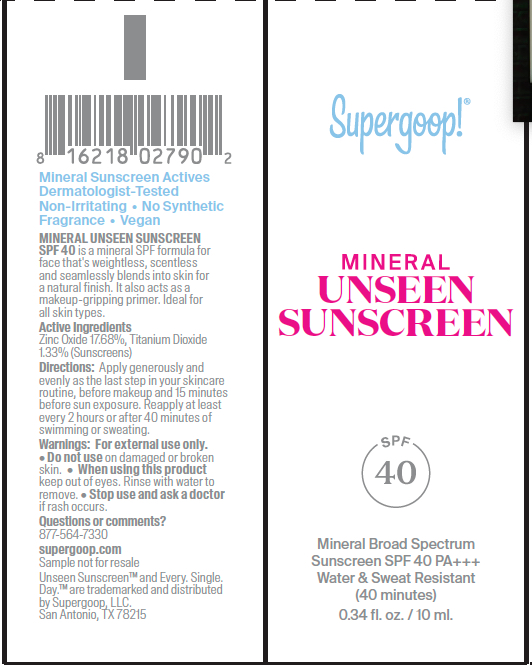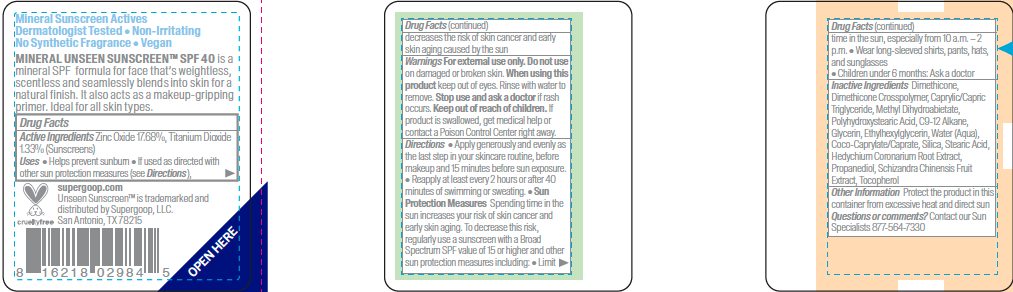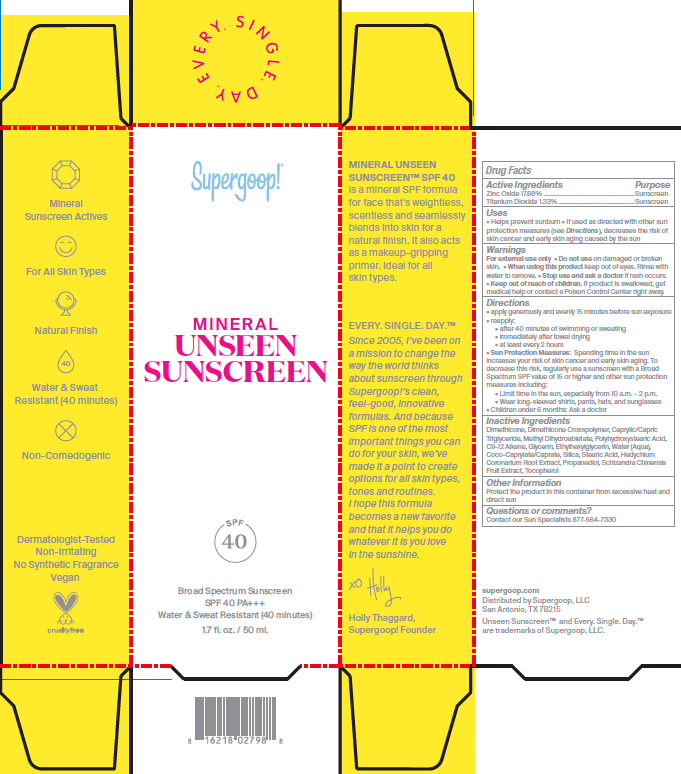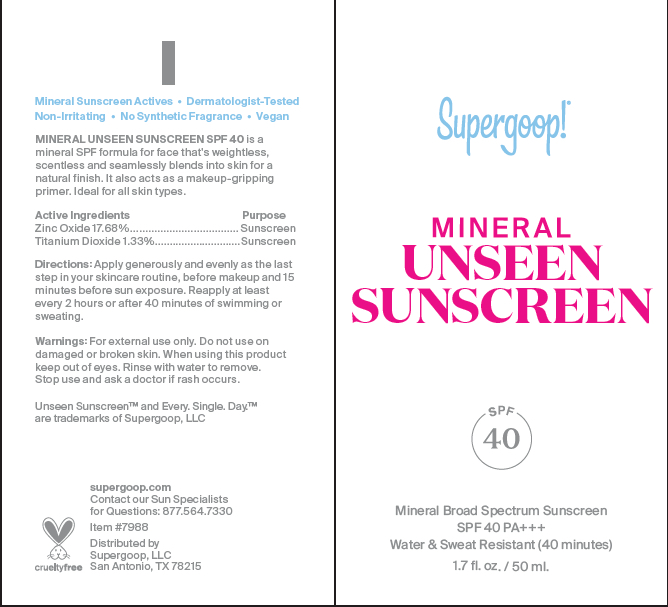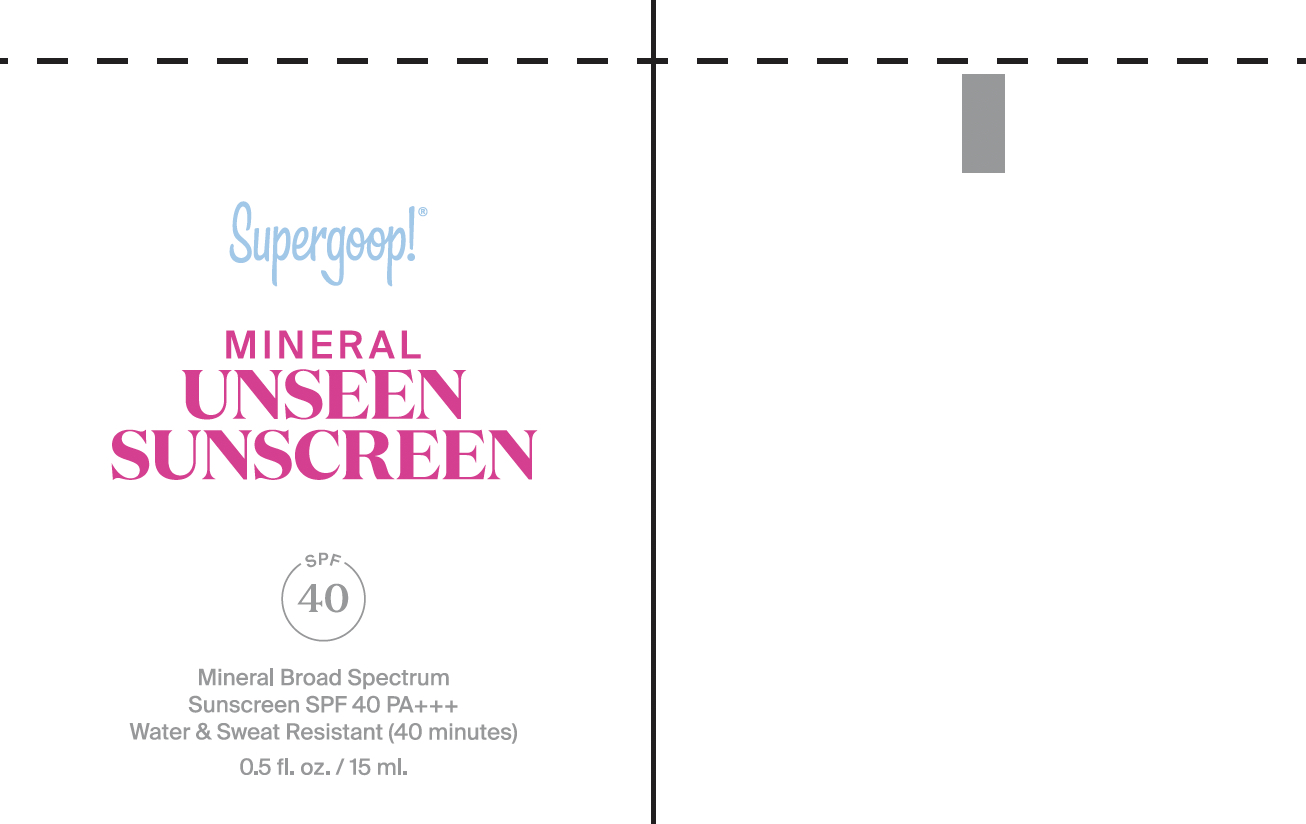 DRUG LABEL: Mineral Unseen Sunscreen SPF 40
NDC: 75936-623 | Form: LOTION
Manufacturer: Supergoop, LLC
Category: otc | Type: HUMAN OTC DRUG LABEL
Date: 20240223

ACTIVE INGREDIENTS: ZINC OXIDE 17.68 g/100 mL; TITANIUM DIOXIDE 1.33 g/100 mL
INACTIVE INGREDIENTS: DIMETHICONE; C9-12 ALKANE; HEDYCHIUM CORONARIUM ROOT; TOCOPHEROL; GLYCERIN; WATER; METHYL DIHYDROABIETATE; COCO-CAPRYLATE/CAPRATE; STEARIC ACID; POLYHYDROXYSTEARIC ACID (2300 MW); SILICON DIOXIDE; ETHYLHEXYLGLYCERIN; MEDIUM-CHAIN TRIGLYCERIDES; PROPANEDIOL; SCHISANDRA CHINENSIS FRUIT; DIMETHICONE CROSSPOLYMER (450000 MPA.S AT 12% IN CYCLOPENTASILOXANE)

Mineral Unseen Sunscreen SPF 40

ACTIVE INGREDIENT

Active Ingredients: Titanium Dioxide 1.33%, Zinc Oxide 17.68%

PURPOSE

Helps prevent sunburn

If used as directed with other sun protection measures (see Directions), decreases the risk of skin cancer and early skin aging caused by the sun

Keep out of reach of children. If product is swallowed, get medical help, or contact a poison control center right away.

WARNINGS

For External use only

Do not use on damaged or broken skin

When using this product, keep out of eyes. Rinse with water to remove

Stop use and ask a doctor if rash occurs

Directions

Apply generously and evenly 15 minutes before sun exposure

Reapply (will vary depending on WR)

after XX minutes of swimming or sweating

Immediately after towel drying

at least every 2 hours

Sun Protection Measures: Spending time in the sun increases your risk of skin cancer and early skin aging. To decrease this risk, regularly use a sunscreen with a Broad Spectrum SPF value of 15 or higher and other sun protection measures including:

Limit time in the sun, especially from 10 a.m.- 2 p.m.

Wear long-sleeved shirts, pants, hats, and sunglasses

Children under 6 months: Ask a doctor

INACTIVE INGREDIENT

Inactive Ingredients: DIMETHICONE, DIMETHICONE CROSSPOLLYMER, CAPRYLIC/CAPRIC TRIGLYCERIDE, METHYL DIHYDROABIETATE, POLYHYDROXYSTEARIC ACID, C9-12 ALKANE, GLYCERIN, ETHYLHEXYLGLYCERIN, WATER (AQUA), COCO-CAPRYLATE/CAPRATE, SILICA, STEARIC ACID, HEDYCHIUM CORONARIUM ROOT EXTRACT, PROPANEDIOL, SCHIZANDRA CHINENSIS FRUIT EXTRACT, TOCOPHEROL

PACKAGE LABEL

Mineral Unseen Sunscreen SPF 40

Broad Spectrum Sunscreen

1.7 fl. oz. / 50 ml

Mineral Unseen Sunscreen SPF 40

15 mL

Mineral Unseen Sunscreen SPF 40

10 ml

Mineral Unseen Sunscreen SPF 40

1.5 ml